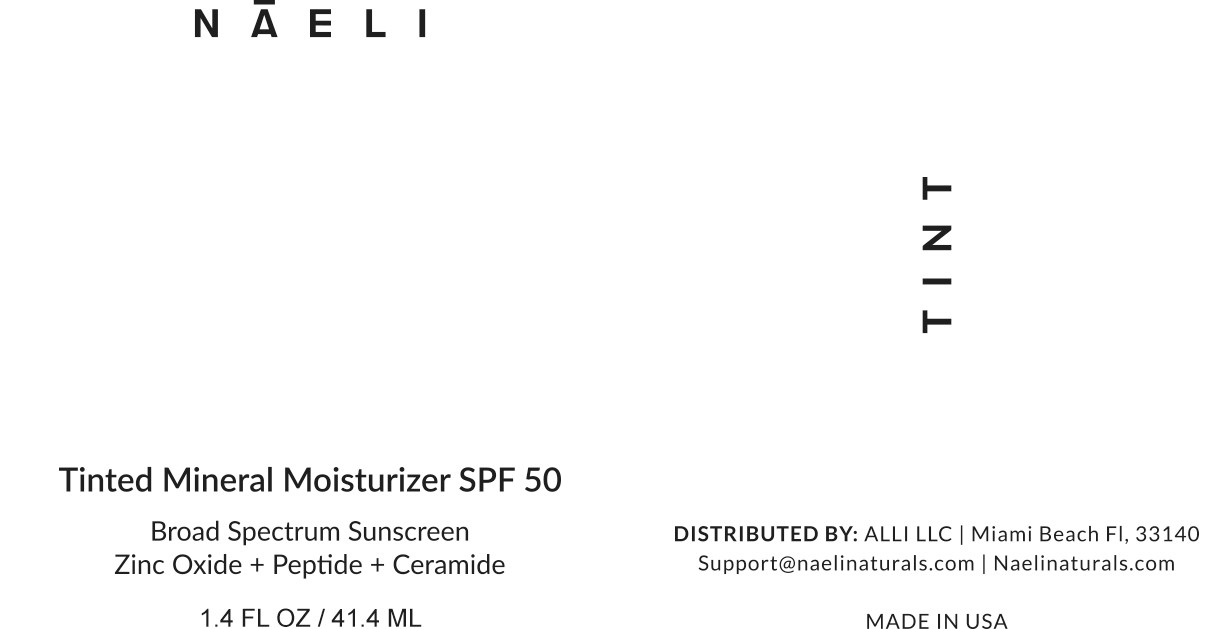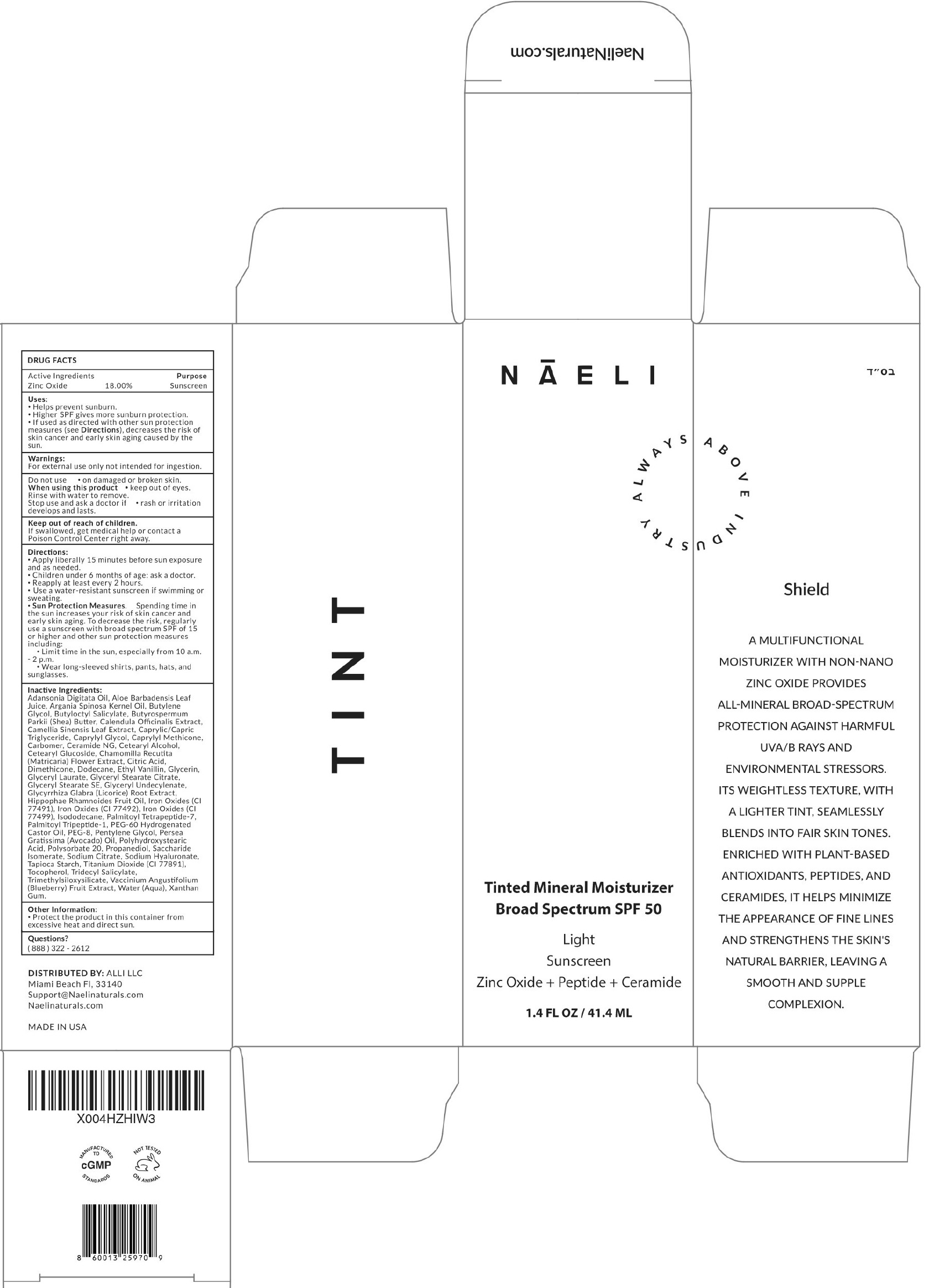 DRUG LABEL: NAELI Tinted Mineral Moisturizer Sunscreen SPF 50, Light
NDC: 73670-609 | Form: LIQUID
Manufacturer: ALLI LLC
Category: otc | Type: HUMAN OTC DRUG LABEL
Date: 20250522

ACTIVE INGREDIENTS: ZINC OXIDE 180 mg/1 mL
INACTIVE INGREDIENTS: ADANSONIA DIGITATA SEED OIL; ALOE VERA LEAF; ARGAN OIL; BUTYLENE GLYCOL; BUTYLOCTYL SALICYLATE; SHEA BUTTER; CALENDULA OFFICINALIS FLOWER; GREEN TEA LEAF; MEDIUM-CHAIN TRIGLYCERIDES; CAPRYLYL GLYCOL; CAPRYLYL METHICONE; CARBOMER HOMOPOLYMER, UNSPECIFIED TYPE; CERAMIDE NG; CETEARYL ALCOHOL; CETEARYL GLUCOSIDE; CHAMOMILE; CITRIC ACID MONOHYDRATE; DIMETHICONE; DODECANE; ETHYL VANILLIN; GLYCERIN; GLYCERYL LAURATE; GLYCERYL STEARATE CITRATE; GLYCERYL STEARATE SE; GLYCYRRHIZA GLABRA (LICORICE) ROOT POWDER; HIPPOPHAE RHAMNOIDES FRUIT OIL; FERRIC OXIDE RED; FERRIC OXIDE YELLOW; FERROSOFERRIC OXIDE; ISODODECANE; PALMITOYL TETRAPEPTIDE-7; PALMITOYL TRIPEPTIDE-1; PEG-60 HYDROGENATED CASTOR OIL; POLYETHYLENE GLYCOL 400; PENTYLENE GLYCOL; PERSEA GRATISSIMA (AVOCADO) OIL; POLYSORBATE 20; PROPANEDIOL; SACCHARIDE ISOMERATE; SODIUM CITRATE; SODIUM HYALURONATE; TAPIOCA STARCH; TITANIUM DIOXIDE; TOCOPHEROL; TRIDECYL SALICYLATE; LOWBUSH BLUEBERRY; WATER; XANTHAN GUM

NAELI Tinted Mineral Moisturizer Sunscreen SPF 50, Light

Active Ingredients

Zinc Oxide 18.00%

Purpose

Sunscreen

Uses:

- Helps prevent sunburn.
- Higher SPF gives more sunburn protection.
- If used as directed with other sun protection measures (see Directions), decreases the risk of skin cancer and early skin aging caused by the sun.

Warnings:

For external use only not intended for ingestion.

Do not use

- on damaged or broken skin.

When using this product

- keep out of eyes. Rinse with water to remove.

Stop use and ask a doctor if

rash or irritation develops and lasts.

Keep out of reach of children.

If swallowed, get medical help or contact a Poison Control Center right away.

Directions:

- Apply liberally 15 minutes before sun exposure and as needed.
- Children under 6 months of age: ask a doctor.
- Reapply at least every 2 hours.
- Use a water-resistant sunscreen if swimming or sweating.
- Sun Protection Measures:Spending time in the sun increases your risk of skin cancer and early skin aging. To decrease this risk, regularly use a sunscreen with a broad spectrum SPF of 15 or higher and other sun protection measures including:
- Limit time in the sun, especially from 10 a.m.- 2 p.m.
- Wear long-sleeved shirts, pants, hats, and sunglasses.

Inactive Ingredients:

Adansonia Digitata Oil, Aloe Barbadensis Leaf Extract, Argania Spinosa Kernel Oil, Butylene Glycol, Butyloctyl Salicylate, Butyrospermum Parkii (Shea) Butter, Calendula Officinalis Flower Extract, Camellia Sinensis Leaf Extract, Caprylic/Capric Triglyceride, Caprylyl Glycol, Caprylyl Methicone, Carbomer, Ceramide NG, Cetearyl Alcohol, Cetearyl Glucoside, Chamomilla Recutita (Matricaria) Flower Extract, Citric Acid, Dimethicone, Dodecane, Ethyl Vanillin, Glycerin, Glyceryl Laurate, Glyceryl Stearate Citrate, Glyceryl Stearate SE, Glyceryl Undecylenate, Glycyrrhiza Glabra (Licorice) Root Extract, Hippophae Rhamnoides Fruit Oil, Iron Oxides (CI 77491), Iron Oxides (CI 77492), Iron Oxides (CI 77499), Isododecane, Palmitoyl Tetrapeptide-7, Palmitoyl Tripeptide-1, PEG-60 Hydrogenated Castor Oil, PEG-8, Pentylene Glycol, Persea Gratissima (Avocado) Oil, Polyhydroxystearic Acid, Polysorbate 20, Propanediol, Saccharide Isomerate, Sodium Citrate, Sodium Hyaluronate, Tapioca Starch, Titanium Dioxide (CI 77891), Tocopherol, Tridecyl Salicylate, Trimethylsiloxysilicate, Vaccinium Angustifolium (Blueberry) Fruit Extract, Water (Aqua), Xanthan Gum.

Other Information:

Protect the product in this container from excessive heat and direct sun.

Questions?

(888) 322 - 2612